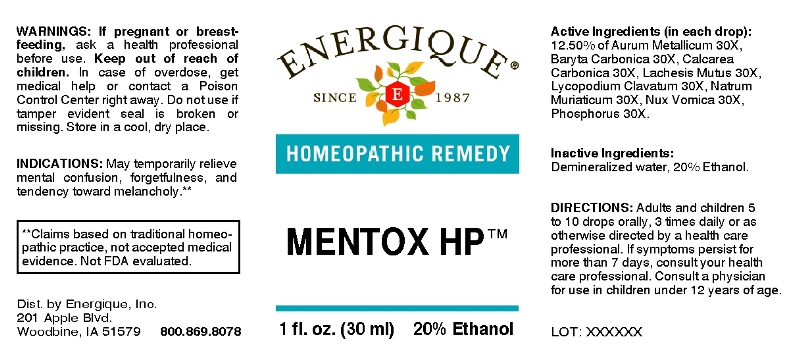 DRUG LABEL: Mentox
NDC: 44911-0299 | Form: LIQUID
Manufacturer: Energique, Inc.
Category: homeopathic | Type: HUMAN OTC DRUG LABEL
Date: 20240528

ACTIVE INGREDIENTS: GOLD 30 [hp_X]/1 mL; BARIUM CARBONATE 30 [hp_X]/1 mL; OYSTER SHELL CALCIUM CARBONATE, CRUDE 30 [hp_X]/1 mL; LACHESIS MUTA VENOM 30 [hp_X]/1 mL; LYCOPODIUM CLAVATUM SPORE 30 [hp_X]/1 mL; SODIUM CHLORIDE 30 [hp_X]/1 mL; STRYCHNOS NUX-VOMICA SEED 30 [hp_X]/1 mL; PHOSPHORUS 30 [hp_X]/1 mL
INACTIVE INGREDIENTS: WATER; ALCOHOL

DRUG FACTS:

ACTIVE INGREDIENTS:

(in each drop): 12.50% Aurum Metallicum 30X, Baryta Carbonica 30X, Calcarea Carbonica 30X, Lachesis Mutus 30X, Lycopodium Clavatum 30X, Natrum Muriaticum 30X, Nux Vomica 30X, Phosphorus 30X.

INDICATIONS:

May temporarily relieve mental confusion, forgetfulness, and tendency toward melancholy.**

**Claims based on traditional homeopathic practice, not accepted medical evidence. Not FDA evaluated.

WARNINGS:

If pregnant or breastfeeding, ask a health professional before use.
Keep out of reach of children. In case of overdose, get medical help or contact a Poison Control Center right away.
Do not use if tamper evident seal is broken or missing.
Store in a cool, dry place.

KEEP OUT OF REACH OF CHILDREN:

In case of overdose, get medical help or contact a Poison Control Center right away.

DIRECTIONS:

Adults and children 5 to 10 drops orally, 3 times daily or as otherwise directed by a health care professional. If symptoms persist for more than 7 days, consult your health care professional. Consult a physician for use in children under 12 years of age.

INDICATIONS:

May temporarily relieve mental confusion, forgetfulness, and tendency toward melancholy.**

**Claims based on traditional homeopathic practice, not accepted medical evidence. Not FDA evaluated.

INACTIVE INGREDIENTS:

Demineralized water, 20% Ethanol.

QUESTIONS:

Dist. by Energique, Inc.
201 Apple Blvd.
Woodbine, IA 51579 800.868.8078

PACKAGE LABELDISPLAY:

ENERGIQUE

SINCE 1987

HOMEOPATHIC REMEDY

MENTOX HP

1 fl. oz. (30 ml)